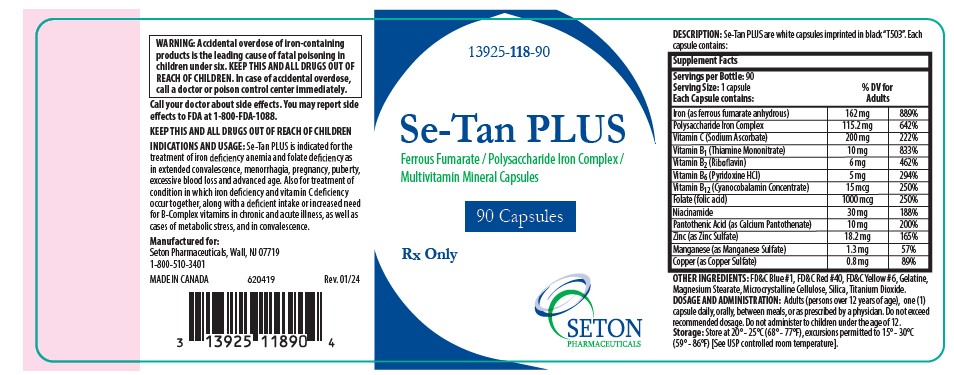 DRUG LABEL: Se-Tan PLUS
NDC: 13925-118 | Form: CAPSULE, GELATIN COATED
Manufacturer: Seton Pharmaceuticals
Category: prescription | Type: HUMAN PRESCRIPTION DRUG LABEL
Date: 20250424

ACTIVE INGREDIENTS: FERROUS FUMARATE 162 mg/1 1; IRON DEXTRAN 115.2 mg/1 1; SODIUM ASCORBATE 200 mg/1 1; THIAMINE MONONITRATE 10 mg/1 1; RIBOFLAVIN 6 mg/1 1; PYRIDOXINE HYDROCHLORIDE 5 mg/1 1; CYANOCOBALAMIN 15 ug/1 1; FOLIC ACID 1 mg/1 1; NIACINAMIDE 30 ug/1 1; CALCIUM PANTOTHENATE 10 mg/1 1; ZINC SULFATE  18.2 mg/1 1; MANGANESE SULFATE 1.3 mg/1 1; CUPRIC SULFATE 0.8 mg/1 1
INACTIVE INGREDIENTS: FD&C BLUE NO. 1; FD&C RED NO. 40; FD&C YELLOW NO. 6; GELATIN; MAGNESIUM STEARATE; CELLULOSE, MICROCRYSTALLINE; SILICON DIOXIDE; TITANIUM DIOXIDE

Se-Tan PLUS

Ferrous Fumarate / Polysaccharide Iron Complex / Multivitamin Mineral Capsules

Rx Only

DESCRIPTION

DESCRIPTION: Se-Tan PLUS are white capsules imprinted in black "T503". Each capsule contains:

Supplement Facts
Servings per Bottle: 90; Serving Size: 1 capsule; Each Capsule contains: | %DV for; Adults
Iron (as ferrous fumarate anhydrous) | 32.5 mg | 181%
Polysaccharide Iron Complex | 115.2 mg | 642%
Vitamin C (Sodium Ascorbate) | 200 mg | 222%
Vitamin B1 (Thiamine Mononitrate) | 10 mg | 833%
Vitamin B2 (Riboflavin) | 6 mg | 462%
Vitamin B6 (Pyridoxine HCl) | 5 mg | 294%
Vitamin B12 (Cyanocobalamin Concentrate) | 15 mcg | 250%
Folate (folic acid) | 1000 mcg | 250%
Niacinamide | 30 mg | 188%
Pantothenic Acid (as Calcium Panothenate) | 10 mg | 200%
Zinc (as Zinc Sulfate) | 18.2 mg | 165%
Manganese (as Manganese Sulfate) | 1.3 mg | 57%
Copper (as Copper Sulfate) | 0.8 mg | 89%

OTHER INGREDIENTS

FD&C Blue #1, FD&C Red #40, FD&C Yellow #6, Gelatine, Magnesium Stearate, Microcrystalline Cellulose, Silica, Titanium Dioxide.

CLINICAL PHARMACOLOGY

Oral iron is absorbed most efficiently when administered between meals. Iron is critical for normal hemoglobin synthesis to maintain oxygen transport, energy production and proper function of cells. Adequate amounts of iron are necessary for effective erythropoiesis. Iron also serves as a cofactor of several essential enzymes, including cytochromes, which are involved in electron transport. Folic acid is required for nucleoprotein synthesis and the maintenance of normal eryhtropoiesis. Folic acid is the precursor of tetrahydrofolic acid, which is involved as a cofactor for transformylation reactions in the biosynthesis of purines and thymidylates of nucleic acids. Deficiency of folic acid may account for the defective deoxyribonucleic acid (DNA) synthesis that leads to megaloblast formation and megaloblasticmacrocytic anemias. Vitamin B12 is essential to growth, cell reproduction, hematopoiesis, nucleic acid, and mylein synthesis. Deficiency may result in megaloblastic anemia or pernicious anemia.

INDICATIONS AND USAGE:

Se-Tan PLUS is indicated for the treatment of iron deficiency anemia and folate deficiency as in extended convalescence, menorrhagia, pregnancy, puberty, excessive blood loss and advanced age. Also for treatment of condition in which iron deficiency and vitamin C deficiency occur together, along with a deficient intake or increased need for B-Complex vitamins in chronic and acute illness, as well as cases of metabolic stress, and in convalescence.

CONTRAINDICATIONS:

Se-Tan PLUS is contraindicated in patients with a known hypersensitivity to any of its ingredients; also, all iron compounds are contraindicated in patients with hemosiderosis, hemochromatosis, or hemolytic anemias. Pernicious anemia is a contraindication, as folic acid may obscure its signs and symptoms.

WARNING: Folic acid alone is improper therapy in the treatment of pernicious anemia and other megaloblastic anemias where Vitamin B12 is deficient.

BOXED WARNING

WARNING: Accidental overdose of iron-containing products is the leading cause of fatal poisoning in children under six. Keep this and all drugs out of reach of children. In case of accidental overdose, call a doctor or poison control center immediately.

GENERAL PRECAUTIONS

General: Folic acid in doses above 0.1 mg - 0.4 mg daily may obscure pernicious anemia, in that hematological remission can occur while neurological manifestations remain progressive.

PEDIATRIC USE

Pediatric Use: Safety and effectiveness of this product have not been established in pediatric patients.

GERIATRIC USE

Geriatric Use: No clinical studies have been performed in patients age 65 and over to determine whether older persons respond differently from younger persons. Dosage should always begin at the low end of the dosage scale and should consider that elderly persons may have decreased hepatic, renal, or cardiac function and or concomitant diseases.

ADVERSE REACTIONS:

Folic Acid: Allergic sensitizations have been reported following both oral and parenteral administration of folic acid.

Ferrous Fumarate: Gastrointestinal disturbances (anorexia, nausea, diarrhea, constipation) occur occasionally, but are usually mild and may subside with continuation of therapy. Although the absorption of iron is best when taken between meals, giving Se-Tan PLUS after meals may control occasional G.I. disturbances. Se-Tan PLUS is best absorbed when taken at bedtime.

DRUG INTERACTIONS

Prescriber should be aware of a number of iron/drug interactions, including antacids, tetracyclines, or fluoroquinolones.

OVERDOSE:

Iron: Signs and Symptoms: Iron is toxic. Acute overdosage of iron may cause nausea and vomiting and, in severe cases, cardiovascular collapse and death. Other symptoms include pallor and cyanosis, melena, shock, drowsiness and coma. The estimated overdose of orally ingested iron is 300-mg/kg body weight. When overdoses are ingested by children, severe reactions, including fatalities, have resulted. Se-Tan PLUS should be stored beyond the reach of children to prevent against accidental iron poisoning. Keep this and all other drugs out of the reach of children.

Treatment: For specific therapy, exchange transfusion and chelating agents should be used. For general management, perform gastric lavage with sodium bicarbonate solution or milk. Administer intravenous fluids and electrolytes and use oxygen.

DOSAGE AND ADMINISTRATION:

Adults (persons over 12 years of age), one (1) capsule daily, orally, between meals, or as prescribed by a physician. Do not exceed recommended dosage. Do not administer to children under the age of 12.

HOW SUPPLIED:

Se-Tan PLUS are white capsules imprinted in black "T503". Child resistant bottles of 90 capsules.

Product Code: NDC 13925-118-90.

PHARMACIST:

Dispense in a tight, light-resistant container as defined in the USP/NF with a child-resistant closure.

Storage:

Store at 20°-25°C (68°-77°F), excursions permitted to 15°-30°C (59°-86°F) [See USP controlled room temperature]. Keep in a cool dry place.

KEEP THIS AND ALL DRUGS OUT OF REACH OF CHILDREN.

Rx Only

RESERVED FOR PROFESSIONAL RECOMMENDATION.

Manufactured for:
Seton Pharmaceuticals
Manasquan, NJ 08736
1-800-510-3401
MADE IN CANADA
Code 118-90 Rev.03/18

SETON PHARMACEUTICALS

PRINCIPAL DISPLAY PANEL

NDC 13925-118-90

Se-Tan-PLUS

Ferrous Fumarate / Polysaccharide Iron Complex /
Multivitamin Mineral Capsules

90 Capsules

Rx Only

SETON PHARMACEUTICALS